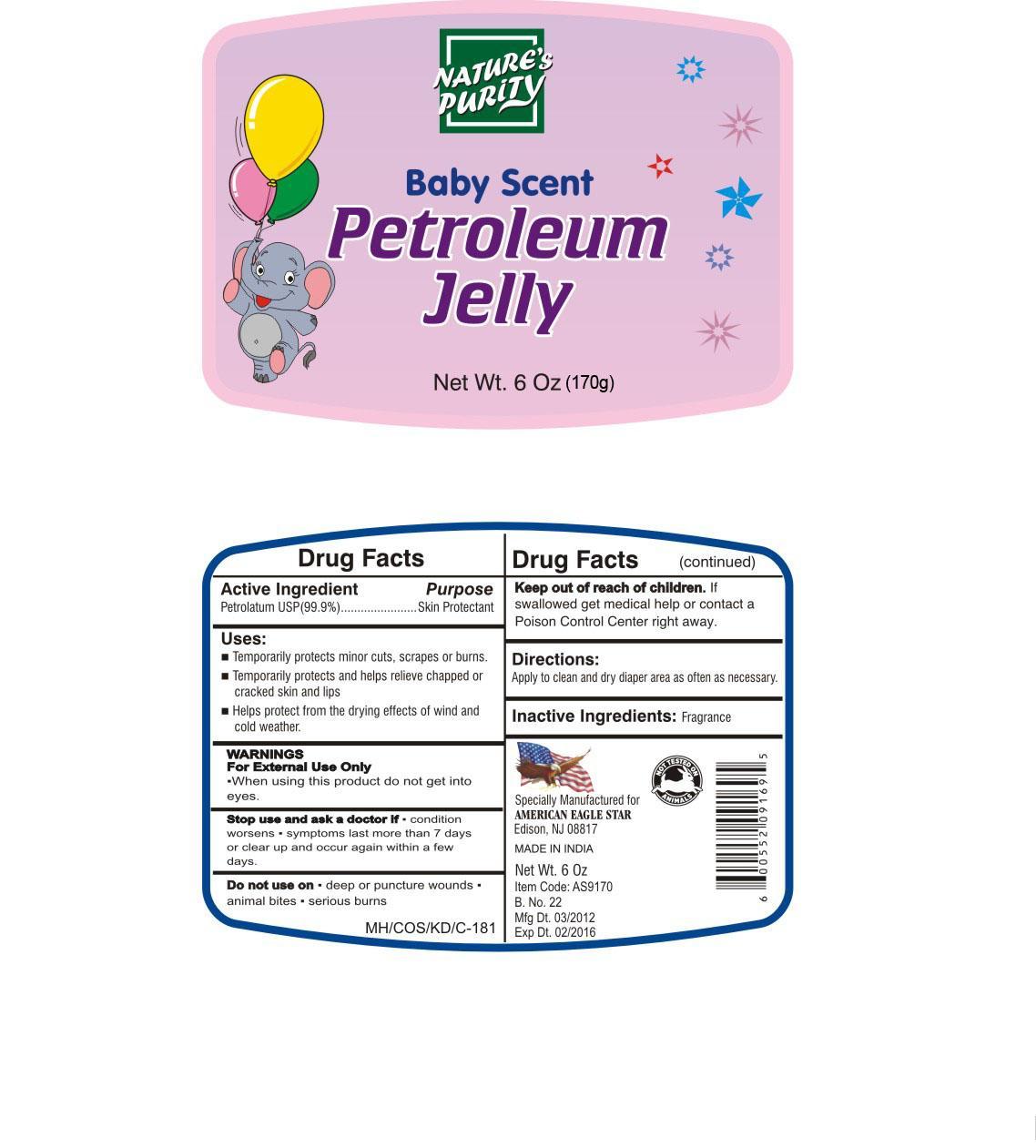 DRUG LABEL: NATURES PURITY
NDC: 52039-001 | Form: OINTMENT
Manufacturer: AMERICAN EAGLE STAR IMPORTS INC.
Category: otc | Type: HUMAN OTC DRUG LABEL
Date: 20120629

ACTIVE INGREDIENTS: PETROLATUM 99.9 g/100 g

Drug Facts

Active IngredientPetrolatum 99.9%

Purpose
Skin protectant

Uses:

- Temporarily protects minor cuts, scrapes or burns.
- Temporarily protects and helps relieve chapped or cracked skin and lips.
- Helps protect from the drying effects of wind and cold weather.

WARNINGS

For external use only.

- When using this product do not get into eyes.

Stop use and ask a doctor if condition worsens symptoms last more than 7 days or clear up and occur again within a few days

Do not use on deep or puncture wounds animal bites serious burns

Keep out of reach of children. If swallowed get medical help or contact a Poison Control Center right away.

Directions:

Apply to a clean and dry diaper area as often as necessary

Inactive ingredients: Fragrance